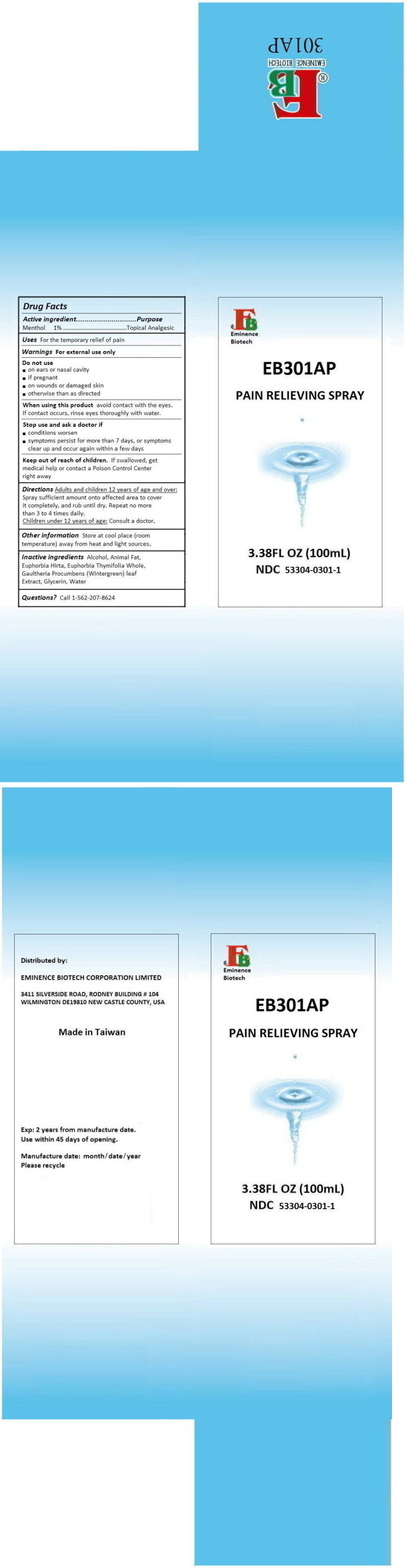 DRUG LABEL: EB301AP PAIN RELIEF
NDC: 53304-0301 | Form: SPRAY
Manufacturer: EMINENCE BIOTECH CORPORATION LIMITED
Category: otc | Type: HUMAN OTC DRUG LABEL
Date: 20180320

ACTIVE INGREDIENTS: MENTHOL, UNSPECIFIED FORM 1000 mg/100 mL
INACTIVE INGREDIENTS: ALCOHOL; EUPHORBIA HIRTA; PORK SIDE BACON, CURED FAT; GAULTHERIA PROCUMBENS LEAF; GLYCERIN; EUPHORBIA THYMIFOLIA WHOLE; WATER

EB301AP PAIN RELIEF

Drug Facts

Active ingredient

Menthol 1%

Purpose

Topical Analgesic

Uses

For the temporary relief of pain

Warnings

For external use only

Do not use

- on ears or nasal cavity
- if pregnant
- on wounds or damaged skin
- otherwise than as directed

When using this product avoid contact with the eyes. If contact occurs, rinse eyes thoroughly with water.

Stop use and ask a doctor if

- conditions worsen
- symptoms persist for more than 7 days, or symptoms clear up and occur again within a few days

Keep out of reach of children. If swallowed, get medical help or contact a Poison Control Center right away.

Directions

Adults and children 12 years of age and over

Spray sufficient amount onto affected area to cover it completely, and rub until dry. Repeat no more than 3 to 4 times daily.

Children under 12 years of age

consult a doctor.

Other information

Store at cool place (room temperature) away from heat and light sources.

Inactive ingredients

Alcohol, Animal Fat, Euphorbia Hirta, Euphorbia Thymifolia Whole, Gaultheria Procumbens (Wintergreen) leaf Extract, Glycerin, Water

Questions?

Call 1-562-207-8624

Distributed by:

EMINENCE BIOTECH CORPORATION LIMITED

3411 SILVERSIDE ROAD, RODNEY BUILDING # 104
WILMINGTON DE19810 NEW CASTLE COUNTY, USA

PRINCIPAL DISPLAY PANEL - 100 mL Bottle Carton

EB
Eminence
Biotech

EB301AP

PAIN RELIEVING SPRAY

3.38FL OZ (100mL)

NDC 53304-0301-1